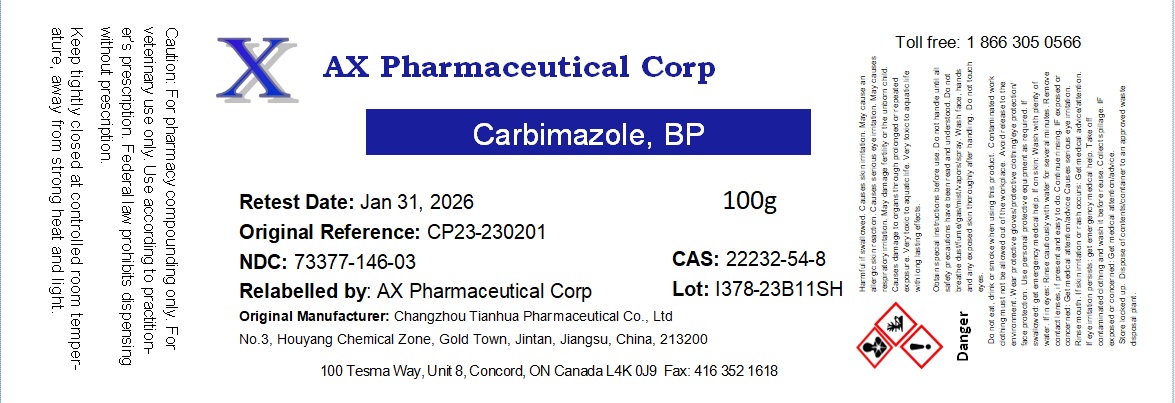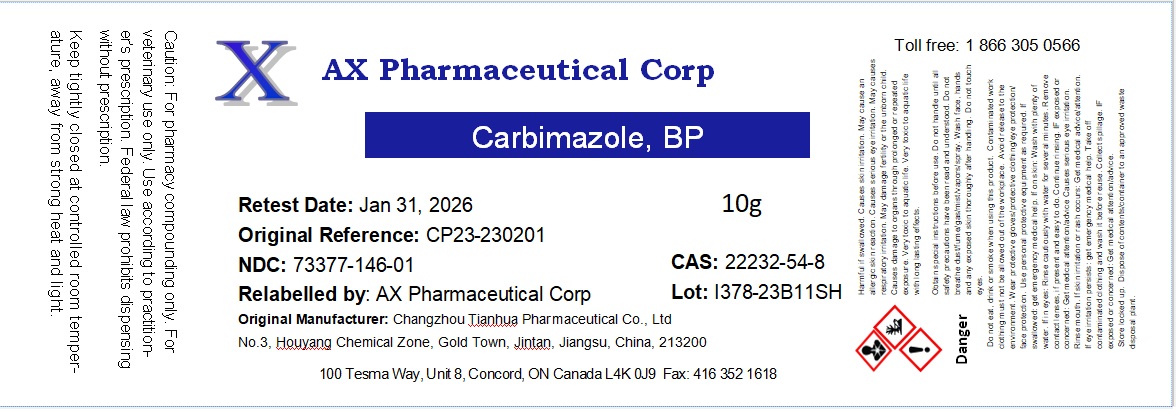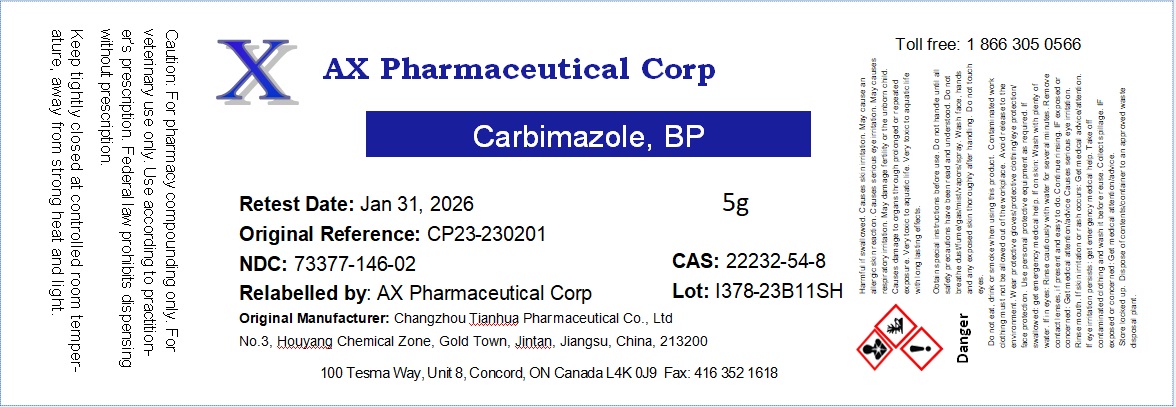 DRUG LABEL: Carbimazole
NDC: 73377-146 | Form: POWDER
Manufacturer: AX Pharmaceutical Corp
Category: other | Type: BULK INGREDIENT - ANIMAL DRUG
Date: 20250703

ACTIVE INGREDIENTS: CARBIMAZOLE 1 g/1 g

Carbimazole